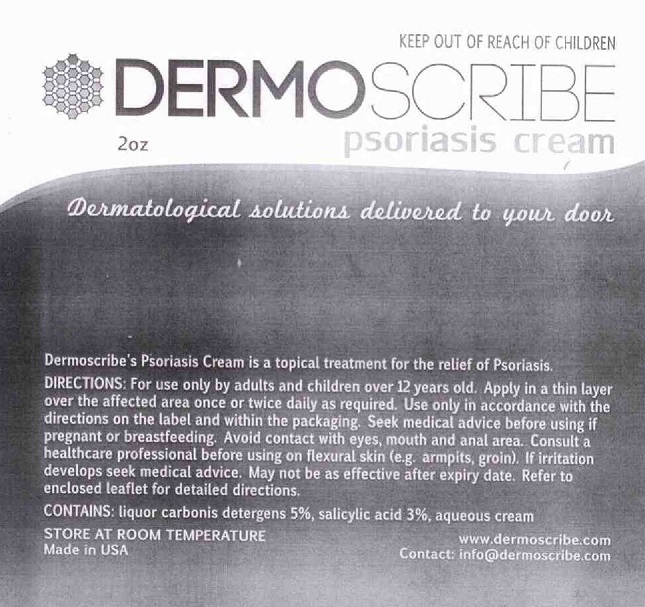 DRUG LABEL: DERMOSCRIBE PSORIASIS
NDC: 69683-201 | Form: CREAM
Manufacturer: DERMOSCRIBE PTY LTD
Category: otc | Type: HUMAN OTC DRUG LABEL
Date: 20221222

ACTIVE INGREDIENTS: COAL TAR 5 g/100 g; SALICYLIC ACID 3 g/100 g
INACTIVE INGREDIENTS: WATER; CARBOMER HOMOPOLYMER TYPE C; MINERAL OIL; GLYCOL STEARATE; SORBITOL; CETOSTEARYL ALCOHOL; STEARIC ACID; GLYCERIN; COCONUT OIL; PROPYLENE GLYCOL; POLYSORBATE 20; SODIUM HYDROXIDE

DERMOSCRIBE - PSORIASIS CREAM (69683-201)

ACTIVE INGREDIENTS

LIQUOR CARBONIS DETERGENS 5%, Salicylic Acid 3%

PURPOSE

TREATMENT OF PSORIASIS.

USE

Dermoscribe's Psoriasis Cream is a topical treatment for relief of Psoriasis.

WARNINGS

FOR EXTERNAL USE ONLY.

Seek medical advice before using if pregnant or breastfeeding. If irritation
develops, stop using and seek medical advice. May not be as effective after expiry date.

KEEP OUT OF REACH OF CHILDREN.

DIRECTIONS

For use only by persons over 12 years old. Apply in a thin layer over the affected area once or twice daily as required.

Use only in accordance with the directions on the label and within the packaging. Refer to enclosed leaflet for detailed directions.

INACTIVE INGREDIENTS

AQUEOUS CREAM

OTHER SAFETY INFORMATION

STORE AT ROOM TEMPERATURE